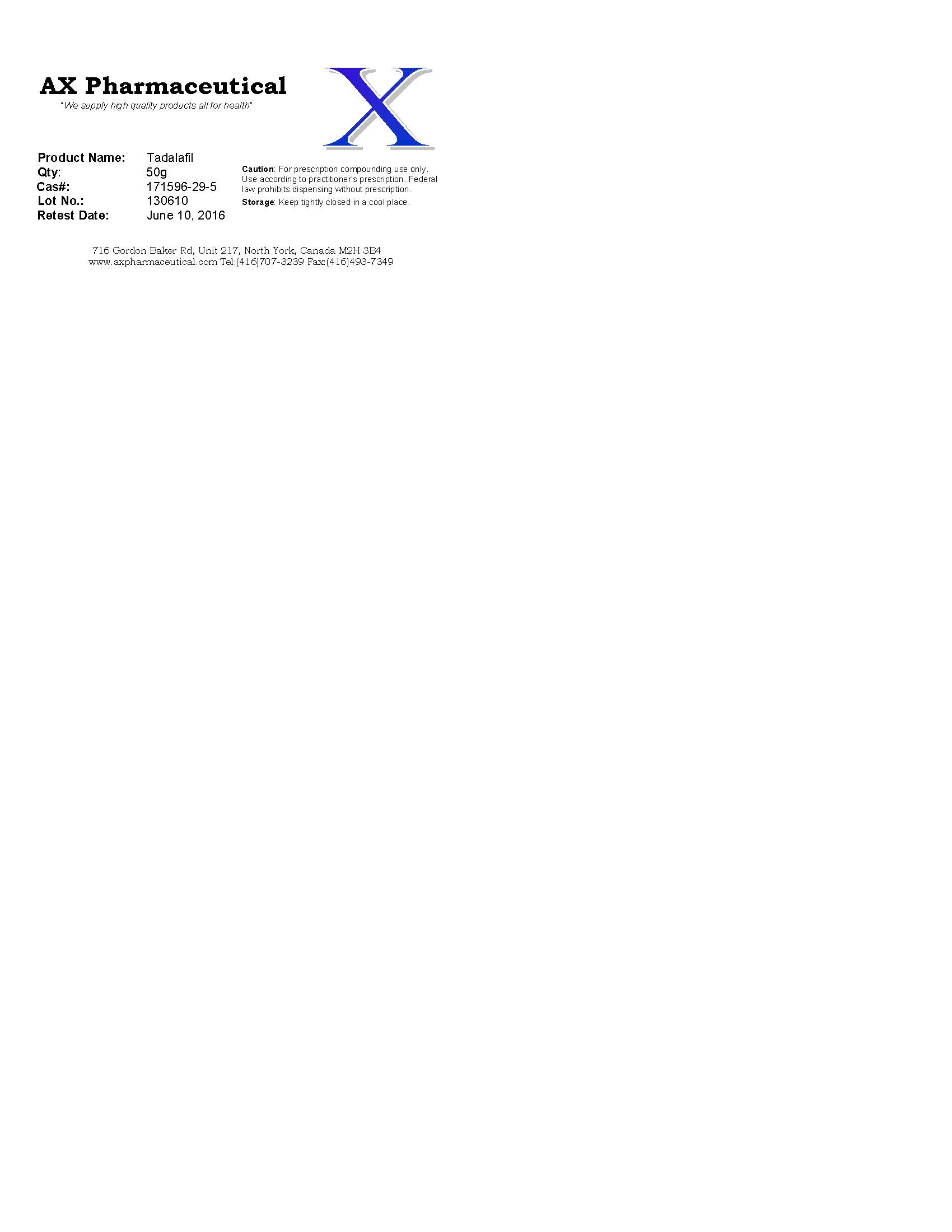 DRUG LABEL: AX Pharmaceutical
                
                
                
                
NDC: 62157-009 | Form: POWDER
Manufacturer: AX Pharmaceutical Corp
Category: other | Type: BULK INGREDIENT
Date: 20160531

ACTIVE INGREDIENTS: TADALAFIL 49 g/50 g
INACTIVE INGREDIENTS: WATER

Drug Facts